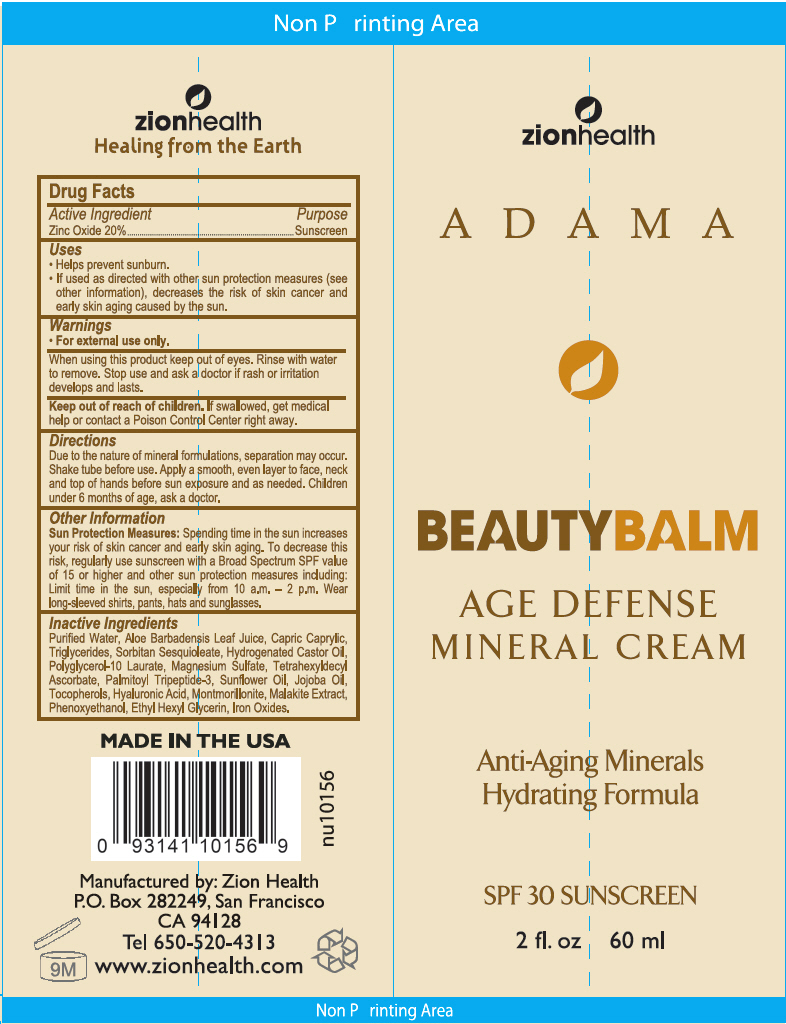 DRUG LABEL: SPF-30 BB
NDC: 69090-0100 | Form: LOTION
Manufacturer: ZION HEALTH
Category: otc | Type: HUMAN OTC DRUG LABEL
Date: 20250113

ACTIVE INGREDIENTS: Zinc Oxide 20 g/100 mL
INACTIVE INGREDIENTS: WATER; ALOE VERA LEAF; SORBITAN SESQUIOLEATE; HYDROGENATED CASTOR OIL; POLYGLYCERYL-10 LAURATE; MAGNESIUM SULFATE, UNSPECIFIED FORM; TETRAHEXYLDECYL ASCORBATE; SUNFLOWER OIL; JOJOBA OIL; TOCOPHEROL; HYALURONIC ACID; MONTMORILLONITE; PHENOXYETHANOL; ETHYLHEXYLGLYCERIN; FERRIC OXIDE RED

SPF-30 BB CREAM

Drug Facts

Active Ingredient

Zinc Oxide 20%

Purpose

Sunscreen

Uses

- Helps prevent sunburn.
- If used as directed with other sun protection measures (see other information) , decreases the risk of skin cancer and early skin aging caused by the sun.

Warnings

- For external use only.

When using this product keep out of eyes. Rinse with water to remove.

Stop use and ask a doctor if rash or irritation develops and lasts.

Keep out of reach of children. If swallowed, get medical help or contact a Poison Control Center right away.

Directions

Due to the nature of mineral formulations, separation may occur. Shake tube before use. Apply a smooth, even layer to face, neck and top of hands before sun exposure and as needed. Children under 6 months of age, ask a doctor.

Other Information

Sun Protection Measures

Spending time in the sun increases your risk of skin cancer and early skin aging. To decrease this risk, regularly use sunscreen with a Broad Spectrum SPF value of 15 or higher and other sun protection measures including: Limit time in the sun, especially from 10 a.m. – 2 p.m. Wear long-sleeved shirts, pants, hats and sunglasses.

Inactive Ingredients

Purified Water, Aloe Barbadensis Leaf Juice, Capric Caprylic, Triglycerides, Sorbitan Sesquioleate, Hydrogenated Castor Oil, Polyglycerol-10 Laurate, Magnesium Sulfate, Tetrahexyldecyl Ascorbate, Palmitoyl Tripeptide-3, Sunflower Oil, Jojoba Oil, Tocopherols, Hyaluronic Acid, Montmorillonite, Malakite Extract, Phenoxyethanol, Ethyl Hexyl Glycerin, Iron Oxides.

Manufactured by: Zion Health
P.O. Box 282249, San Francisco
CA 94128

PRINCIPAL DISPLAY PANEL - 110 mL Tube Label

zionhealth

ADAMA

BEAUTYBALM

AGE DEFENSE
MINERAL CREAM

Anti-Aging Minerals
Hydrating Formula

SPF 30 SUNSCREEN

2 fl. oz
60 ml